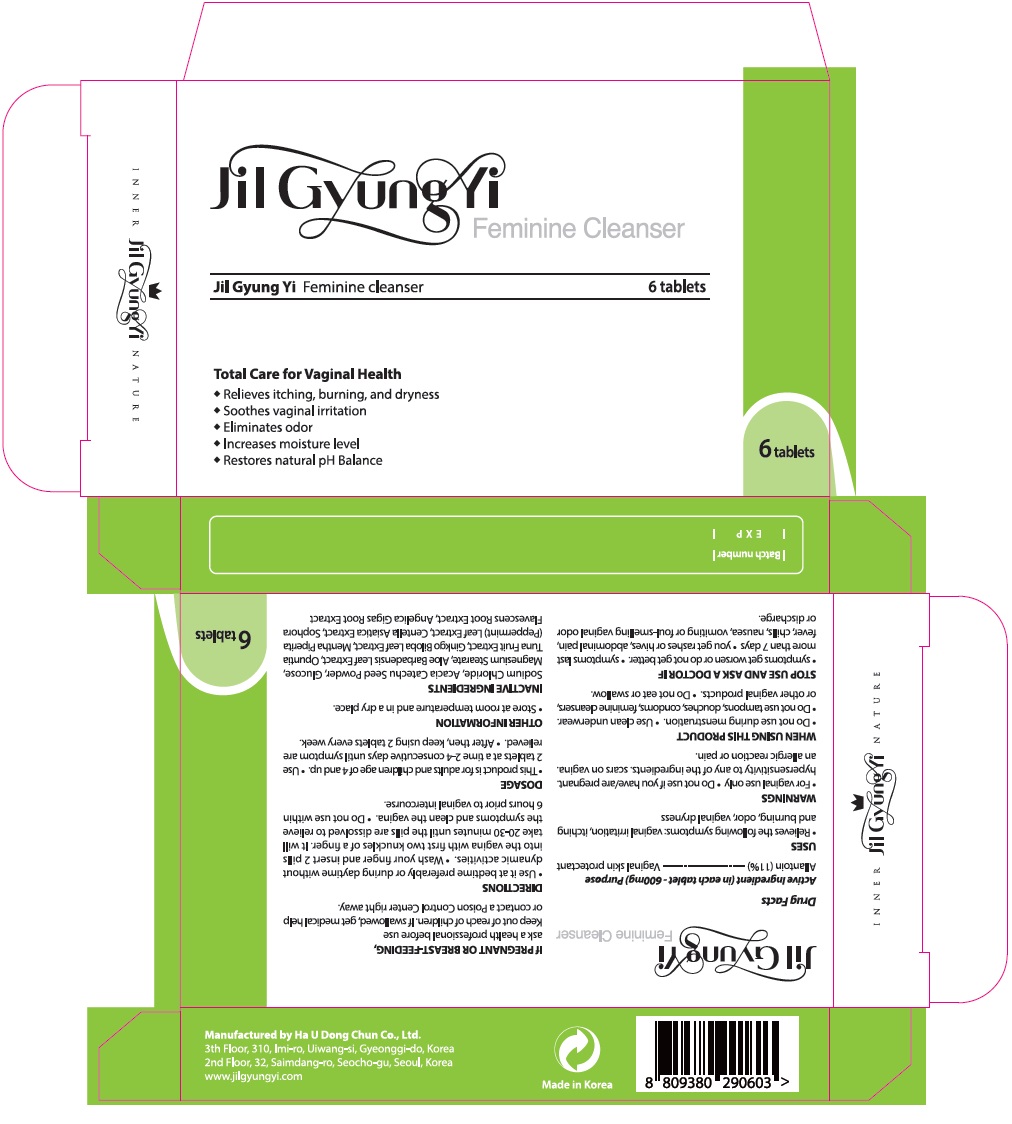 DRUG LABEL: Jilgyungyi (6 Tablets)
NDC: 55618-2007 | Form: TABLET
Manufacturer: Haudongchun Co., Ltd.
Category: otc | Type: HUMAN OTC DRUG LABEL
Date: 20170725

ACTIVE INGREDIENTS: ALLANTOIN 66 mg/600 mg
INACTIVE INGREDIENTS: ANGELICA GIGAS ROOT; SODIUM CHLORIDE; .ALPHA.-D-GLUCOPYRANOSE; MAGNESIUM STEARATE; ALOE VERA LEAF; GINKGO; MENTHA PIPERITA LEAF; CENTELLA ASIATICA; SOPHORA FLAVESCENS ROOT

Jilgyungyi (6 Tablets)

Active Ingredients

Allantoin (11%)

Purpose

Vaginal skin protectant

Keep out of reach of children

If swallowed, get medical help or contact a Poison Control right away. (1-800-222-1222)

Uses

- Moisturizes vaginal dryness and helps to improve elasticity
- Relieves external itching and alleviates odors before and after the menstruation

Directions

For adults – 2 tablets at the same time
- Keep use 2 days consecutively and prefer to use once 10 days in 2 months. (after then, use it when you need)
- Do not use up to 6 hours prior to any sexual relation.
- Do not use up to 6 months after giving birth.
- Symptoms may vary depending on the age of the patient.Directions
- Use only adults and children 12 years age and over
1) Wash hands before using this product
2) Do not remove moisture, open the package and vaginal tablets are placed into the vagina in much the same way as a tampon stand, squat, or lie on your back in a comfortable position then insert the loaded applicator into the vagina as far as it will comfortably go.
3) It is preferable to use the treatment during night time prior to bed.
4) Use of a sanitary pad after application, because there may be vaginal secretion 30min after application. If there are lots of secretion, change a new sanitary pad.
5) Wash the area around the vagina (the vulva) gently next day, bacteria in your vaginal secretion can cause itching.

Warnings

For vaginal use only
Do not use if you have (are)
- an allergic reaction (rashes, and pimples, redness, swelling, skin irritation, discomfort, burning, vaginal peeling or bleeding, pain in the abdomen or pelvic area, fluttering heartbeat and chest pain, lumbar pain, abnormal vaginal secretion, pollakisuria, abnormal dryness, excessive menstrual bleeding, odor and green colored vaginal secretion, hypotension, faint, and papulopustule, pelvic pain)
- pregnant
- hyper sensitive skin and skin ailment
- scars on vagina
- itching, rash, swelling redness, discomfort, burning, irritation vaginal peeling or bleeding
When using this product
- do not use while having the monthly menstrual period
- prior to absorption there is a risk the tablet may fall out of the vagina
- often wash towels or underwear and do not wear reuse underwear again prior to washing due to risk of infections
- try to avoid sexual relations when you have vaginal yeast infection, it can be aggravated
- try not to use tampons and feminine cleansers
- avoid contact with eye area
- do not eat or swallow
- do not use rubber products such as latex, condoms, and diaphragms together
- do not use other vaginal tablets while using Jil Gyung Yi
If pregnant or breast-feeding, do not use.
Store at cool temperature and dry place with a closed container. Avoid direct sunlight
Overdose warning
- If you accidentally take the tablet orally, stop using this medication and see doctor immediately.
Stop use and ask a doctor if you have
- fever (over 36°C), pain in abdomen, odor, lumbar pain, abnormal secretion, nausea and abnormal shoulder pain.

Inactive Ingredients

Sodium Chloride, Soluble Collagen, Glucose, Magnesium Stearate, Aloe Barbadensis Leaf Extract, Cereus Grandiflorus (Cactus) Extract, Ginkgo Biloba Leaf Extract, Mentha Piperita (Peppermint) Leaf Extract, Centella Asiatica Extract, Sophora Flavescens Root Extract, Angelica Gigas Root Extract